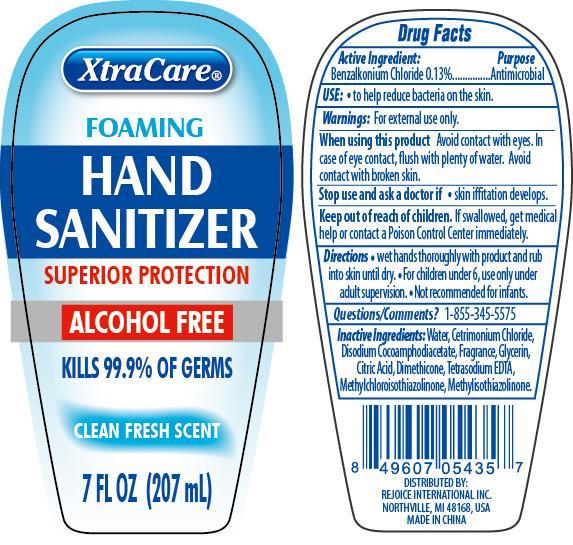 DRUG LABEL: XtraCare Foaming Hand Sanitizer
NDC: 57337-057 | Form: GEL
Manufacturer: Rejoice International
Category: otc | Type: HUMAN OTC DRUG LABEL
Date: 20240228

ACTIVE INGREDIENTS: BENZALKONIUM CHLORIDE 3 g/207 g
INACTIVE INGREDIENTS: WATER; CETRIMONIUM CHLORIDE; DISODIUM COCOAMPHODIACETATE; GLYCERIN; CITRIC ACID MONOHYDRATE; DIMETHICONE; EDETATE SODIUM; METHYLCHLOROISOTHIAZOLINONE; METHYLISOTHIAZOLINONE

XtraCare Foaming Hand Sanitizer

Active Ingredient Purpose

Benzalkonium Chloride 0.13% .......... Antimicrobial

Use:

to help reduce bacteria on the skin

Keep out of reach of children. If swallowed, get medical help or contact a Poison Control Center immediately.

INDICATIONS AND USAGE

XtraCare® Foaming Hand Sanitizer

Superior Protection

Alcohol Free

Kills 99.9% of germs

Clean Fresh Scent

7 FL OZ (207 mL)

Warnings: for external use only.

When using this product Avoid contact with eyes. In case of eye contact, flush with plenty of water. Avoid contact with broken skin.

Stop use and ask a doctor if skin iffitation develops.

Directions

wet hands thoroughly with product and rub into skin until dry.

For children under 6, use only under adult supervision.

Not recommended for infancts.

INACTIVE INGREDIENT

Inactive Ingredients: water, cetrimonium chloride, disodium cocoamphodiacetate, fragrance, glycerin, citric acid, dimethicone, tetrasodium EDTA, methylchloroisothiazolinone, methylisothiazolinone.

OTHER SAFETY INFORMATION

Questions/Comments? 1-855-345-5575

DISTRIBUTED BY:

REJOICE INTERNATIONAL INC

NORTHVILLE, MI 48168 USA

MADE IN CHINA